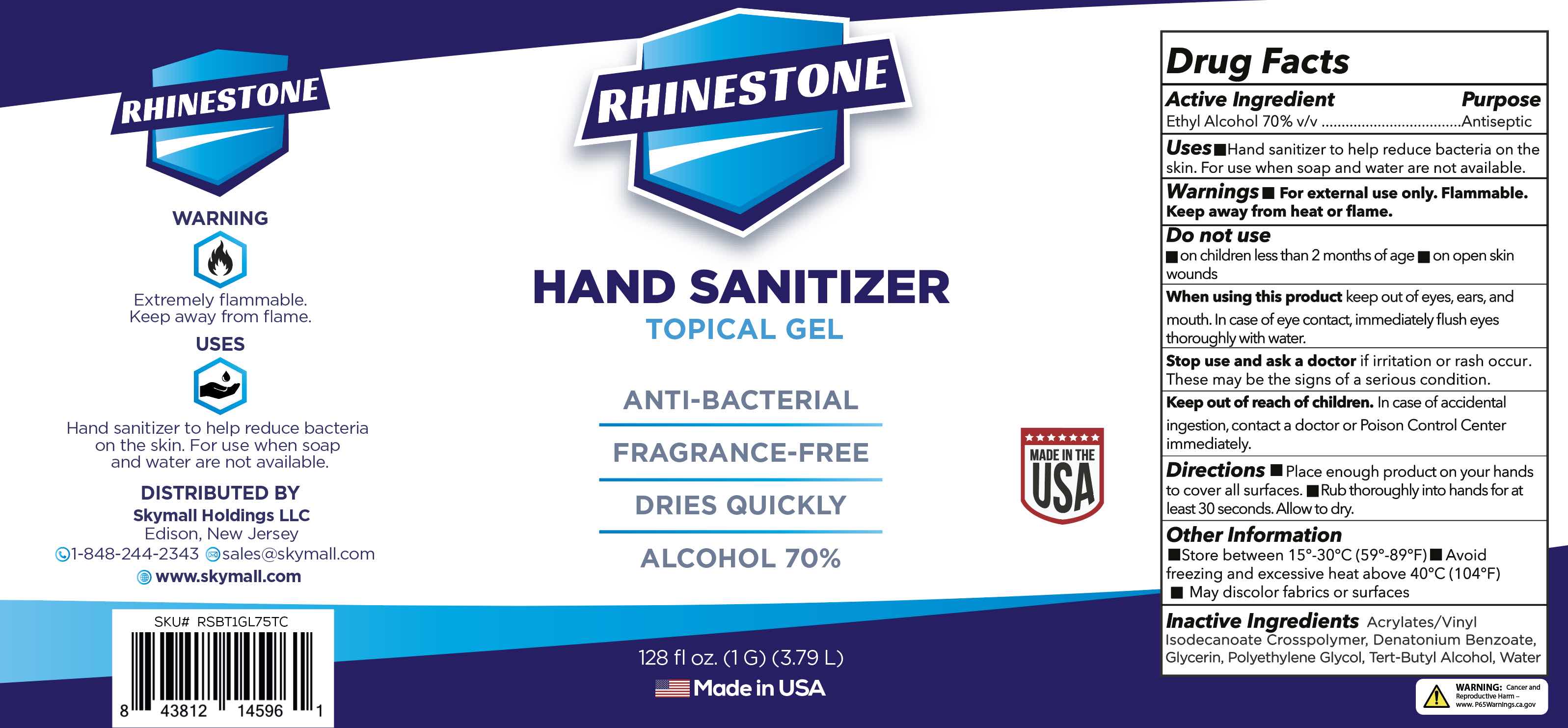 DRUG LABEL: Hand Sanitizer
NDC: 80230-009 | Form: GEL
Manufacturer: Skymall Holdings LLC
Category: otc | Type: HUMAN OTC DRUG LABEL
Date: 20201217

ACTIVE INGREDIENTS: ALCOHOL 70 mL/100 mL
INACTIVE INGREDIENTS: WATER; ACRYLATES/VINYL ISODECANOATE CROSSPOLYMER (10000 MPA.S NEUTRALIZED AT 0.5%); GLYCERIN; DENATONIUM BENZOATE; POLYETHYLENE GLYCOL, UNSPECIFIED; TERT-BUTYL ALCOHOL

Skymall Zink Brntg Rhnstne Sanitizer Gel 70

Active Ingredient

Alcohol 70%v/v

Purpose

Antiseptic

Uses

■ Hand Sanitizer to help reduce bacteria on the skin. For use when soap and water are not available

Warnings

■ For external use only. Flammable. Keep away from heat or flame

Do not use

■ on children less than 2 months of age ■ on open skin wounds

When using this product

keep out of eyes, ears, ears and mouth. In case of eye contact immediately flush eyes thoroughly with water

Stop use and ask a doctor

if irritation or rash occurs. These may be the signs of a serious condition.

Keep out of reach of children

In case of accidentail ingestion, contact a doctor or Poison Control Center immediately.

Directions

■ Place enough product on hands to cover all surfaces. ■Rub thoroughly into hands for at least 30 seconds. Allow to dry.

Other information

■ Store between 15º-30ºC (59º-89ºF) ■ Avoid freezing and excessive heat above 40ºC (104ºF) ■ May discolor fabrics or surfaces.

Inactive ingredients

Acrylates/Vinyl Isodecanoate Crosspolymer, Denatonium Benzoate, Glycerin, Polyethylene Glycol, Tert-Butyl Alcohol, Water